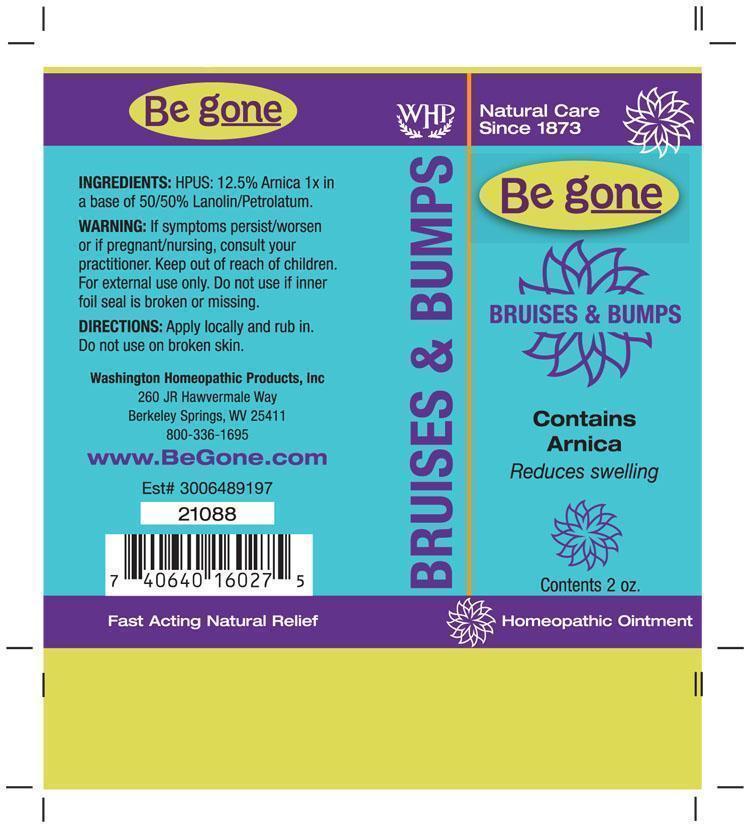 DRUG LABEL: Be gone Bruises and Bumps
NDC: 68428-718 | Form: OINTMENT
Manufacturer: Washington Homeopathic Products
Category: homeopathic | Type: HUMAN OTC DRUG LABEL
Date: 20191223

ACTIVE INGREDIENTS: ARNICA MONTANA 1 [hp_X]/56 g
INACTIVE INGREDIENTS: PETROLATUM; LANOLIN

DRUG FACTS

ACTIVE INGREDIENTS

ARNICA ø

USES

To relieve muscle soreness due to overexertion, bruising from injury. Not for open wounds.

KEEP OUT OF REACH OF CHILDREN

Keep this and all medicines out of reach of children.

INDICATIONS

ARNICA Bruising

STOP USE AND ASK DOCTOR

For external use only. If symptoms persist/worsen or if pregnant/nursing, consult your practitioner.

DIRECTIONS

Apply locally and rub in. Do not use on broken skin.

INACTIVE INGREDIENTS

50% Lanolin

50% Petrolatum

PRINCIPAL DISPLAY PANEL

Be gone Bruises & Bumps tube